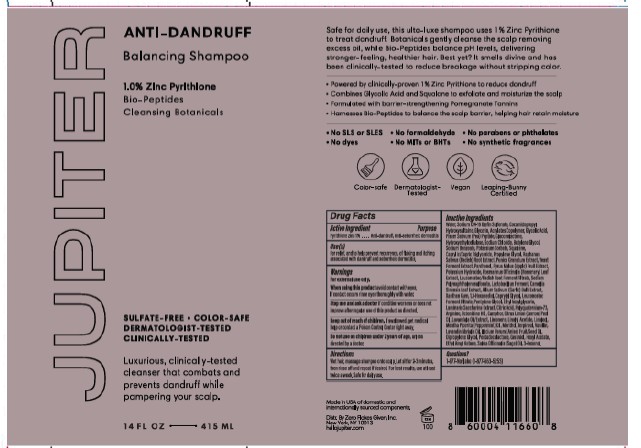 DRUG LABEL: Balancing
NDC: 73528-100 | Form: SHAMPOO
Manufacturer: Zero Flakes Given, Inc.
Category: otc | Type: HUMAN OTC DRUG LABEL
Date: 20250205

ACTIVE INGREDIENTS: PYRITHIONE ZINC 1 g/100 mL
INACTIVE INGREDIENTS: WATER; LEUCONOSTOC/RADISH ROOT FERMENT FILTRATE; ARGININE; ILLICIUM VERUM WHOLE; XANTHAN GUM; HYDROXYETHYLCELLULOSE; PISUM SATIVUM WHOLE; 1,2-HEXANEDIOL; PENTYLENE GLYCOL; POLYQUATERNIUM-73; PUNICA GRANATUM FRUIT JUICE; COCAMIDOPROPYL HYDROXYSULTAINE; LACTOBACILLUS; CAMELLIA SINENSIS LEAF OIL; LINALOOL; VANILLIN; GLYCOLIC ACID; SQUALANE; ETHYLHEXYLGLYCERIN; GLUCONOLACTONE; SODIUM BENZOATE; MENTHOL; 3-OCTANONE; SODIUM MONO- AND DIMETHYL NAPHTHALENE SULFONATES; LAVANDIN OIL; ETHYL ACRYLATE AND METHYL METHACRYLATE COPOLYMER (2:1; 750000 MW); BUTYLENE GLYCOL; PANTHENOL; CITRUS LIMON (LEMON) PEEL OIL; PENTADECALACTONE; CAPRYLYL GLYCOL; OCTENIDINE HCL; CAMPHOR, (-)-; TERPINEOL; GLYCERIN; RAPHANUS SATIVUS VAR. CAUDATUS ROOT; GERANIOL; 3-HEXENOL; ROSMARINUS OFFICINALIS (ROSEMARY) LEAF OIL; CAPRYLIC/CAPRIC TRIGLYCERIDE; YEAST, UNSPECIFIED; PYRUS MALUS (APPLE) JUICE; POTASSIUM HYDROXIDE; ALLIUM SATIVUM (GARLIC) BULB OIL; SACCHARINA LATISSIMA; LINALYL ACETATE; HEXYL ACETATE; SODIUM C14-16 OLEFIN SULFONATE; SODIUM CHLORIDE; CITRIC ACID; LAVANDULA ANGUSTIFOLIA (LAVENDER) OIL; LIMONENE, (+/-)-; MENTHA PIPERITA (PEPPERMINT) OIL; DIPROPYLENE GLYCOL; POTASSIUM SORBATE; PROPYLENE GLYCOL; SALVIA OFFICINALIS (SAGE) OIL

Balancing Shampoo (73528-100)

Active Ingredient

Zinc Pyrithione 1.0%

Purpose

Anti-Dandruff, Anti-seborrheic dermatitis

Uses

For the relief of symptoms from scalp itch, irritation, flaking and redness associated with dandruff.

WARNINGS

For external use only

When using this product avoid contact with eyes. If contact offurs rinse eyes thoroughly with water.

Stop use and ask a doctor if condition worsens or does not improve after regular use of this product as directed.

Keep out of reach of children. If swallowed, get medical help or contact a Poison Control Center right away.

Directions

- Wet hair, massage shampoo onto scalp
- Rinse off and repeat if desired
- For best results, use at least twice a week or as directed by a doctor

Inactive Ingredients

Aqua (Water, Eau), Sodium Cocoyl Isethionate, Sodium Lauroamphoacetate, Acrylates Copolymer, Ethylhexyl Olivate, Stearyl Alcohol, Carthamus Tinctorius (Safflower) Seed Oil, Allium Sativum (Garlic) Bulb Extract, Pyrus Malus (Apple) Fruit Extract, Camellia Sinensis Leaf Extract, Panthenol, Citrus Nobilis (Mandarin Orange) Peel Oil, Foeniculum Vulgare (Fennel) Oil, Lavandula Angustifolia (Lavender) Oil, Mentha Citrata Oil, Orbignya Oleifera Seed Oil, Rosmarinus Officinalis (Rosemary) Leaf Oil, Salvia Sclarea (Clary) Oil, Vanillin, Cocos Nucifera (Coconut) Oil, Laminaria Saccharina Extract, Squalane, Caprylyl Glycol, Yeast Ferment Extract, Guar Hydroxypropyltrimonium Chloride, Glycerin, Sodium Isethionate, Lactobacillus Ferment, Octenidine HCl, Sodium Polynaphthalenesulfonate, Xanthan Gum, Hexamidine Diisethionate, Ethylhexylglycerin, Coconut Alcohol, Raphanus Sativus (Radish) Root Extract, Arginine, Glycolic Acid, Polyquaternium-73, Pentylene Glycol, Propylene Glycol, Sodium Chloride, Potassium Sorbate, Sodium Benzoate, Citric Acid, Linalool

Questions

1-877-No-Flake (1-877-663-5253)